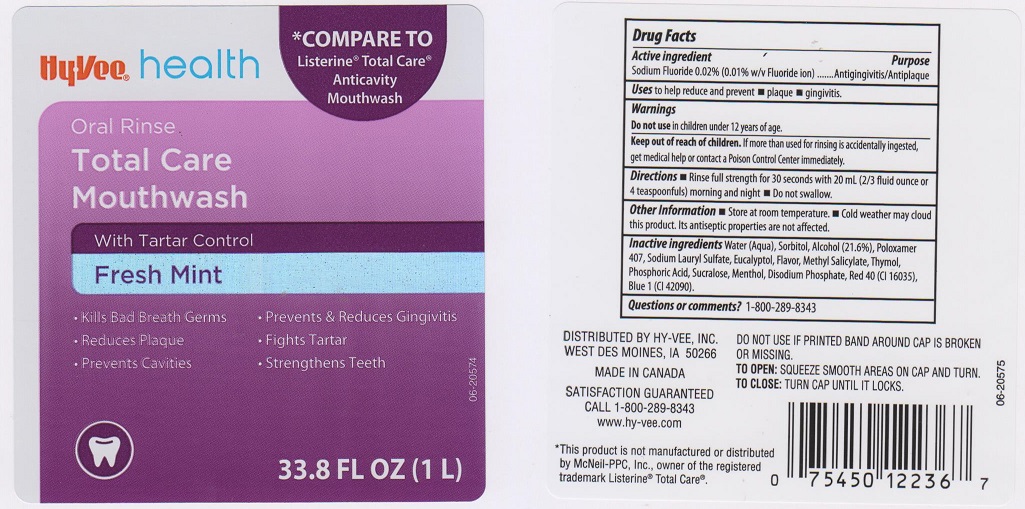 DRUG LABEL: HYVEE
NDC: 42507-552 | Form: LIQUID
Manufacturer: HYVEE INC.
Category: otc | Type: HUMAN OTC DRUG LABEL
Date: 20151127

ACTIVE INGREDIENTS: SODIUM FLUORIDE 0.2 mg/1 mL
INACTIVE INGREDIENTS: WATER; SORBITOL; ALCOHOL; POLOXAMER 407; SODIUM LAURYL SULFATE; EUCALYPTOL; METHYL SALICYLATE; THYMOL; PHOSPHORIC ACID; SUCRALOSE; MENTHOL; SODIUM PHOSPHATE, DIBASIC, ANHYDROUS; FD&C RED NO. 40; FD&C BLUE NO. 1

DRUG FACTS

Active Ingredient

Sodium Fluoride 0.02% (0.01% w/v Fluoride ion)

Purpose

Antigingivitis/Antiplaque

Uses

to help reduce and prevent

- plaque
- gingivitis

Warnings

Do not use in children under 12 years of age

Keep out of reach of children

If more than used for rinsing is accidentally ingested, get medical help or contact a Poison Control Center immediately

Directions

- Rinse full strength for 30 seconds with 20 mL (2/3 fluid ounce or 4 teaspoonfuls) morning and night
- Do not swallow

Other information

- Store at room temperature
- Cold weather may cloud this product. Its antiseptic properties are not affected.

Inactive ingredients

Water (Aqua), Sorbitol, Alcohol (21.6%), Poloxamer 407, Sodium Lauryl Sulfate, Eucalyptol, Flavor, Methyl Salicylate, Thymol, Phosphoric Acid, Sucralose, Menthol, Disodium Phosphate, Red 40 (CI 16035), Blue 1 (CI 42090).

Questions or comments?

1-800-289-8343